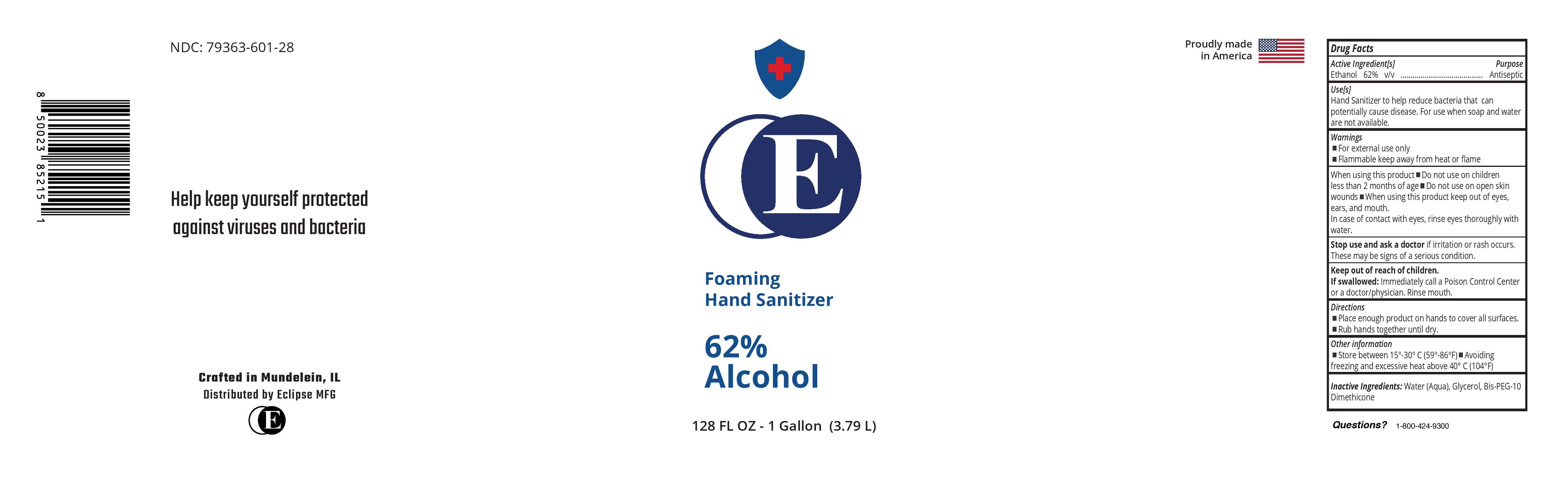 DRUG LABEL: Foaming Hand Sanitizer
NDC: 79363-601 | Form: LIQUID
Manufacturer: REALCHEM MANUFACTURING
Category: otc | Type: HUMAN OTC DRUG LABEL
Date: 20210125

ACTIVE INGREDIENTS: ALCOHOL 54.2 g/100 g
INACTIVE INGREDIENTS: GLYCERIN 0.7188 g/100 g; BIS-PEG-10 DIMETHICONE/DIMER DILINOLEATE COPOLYMER 1.007 g/100 g; WATER

62% Ethanol Foaming HS

This is a foaming hand sanitizer manufactured according to FDA Guidance.

Active Ingredient(s)

Alcohol 62% v/v. Purpose: Antiseptic

Purpose

Antiseptic, Hand Sanitizer

Use

Hand Sanitizer to help reduce bacteria that potentially can cause disease. For use when soap and water are not available.

Warnings

For external use only. Flammable. Keep away from heat or flame

Do not use

- in children less than 2 months of age
- on open skin wounds

When using this product keep out of eyes, ears, and mouth. In case of contact with eyes, rinse eyes thoroughly with water.
Stop use and ask a doctor if irritation or rash occurs. These may be signs of a serious condition.
Keep out of reach of children. If swallowed, get medical help or contact a Poison Control Center right away.

Stop use and ask a doctor if irritation or rash occurs. These may be signs of a serious condition.

Keep out of reach of children. If swallowed, get medical help or contact a Poison Control Center right away.

Directions

- Place enough product on hands to cover all surfaces. Rub hands together until dry.
- Supervise children under 6 years of age when using this product to avoid swallowing.

Other information

- Store between 15-30C (59-86F)
- Avoid freezing and excessive heat above 40C (104F)

Inactive ingredients

glycerin, Bis-PEG-10 Dimethicone, purified water USP

Package Label - Principal Display Panel

3789 mL NDC: 79363-601-28